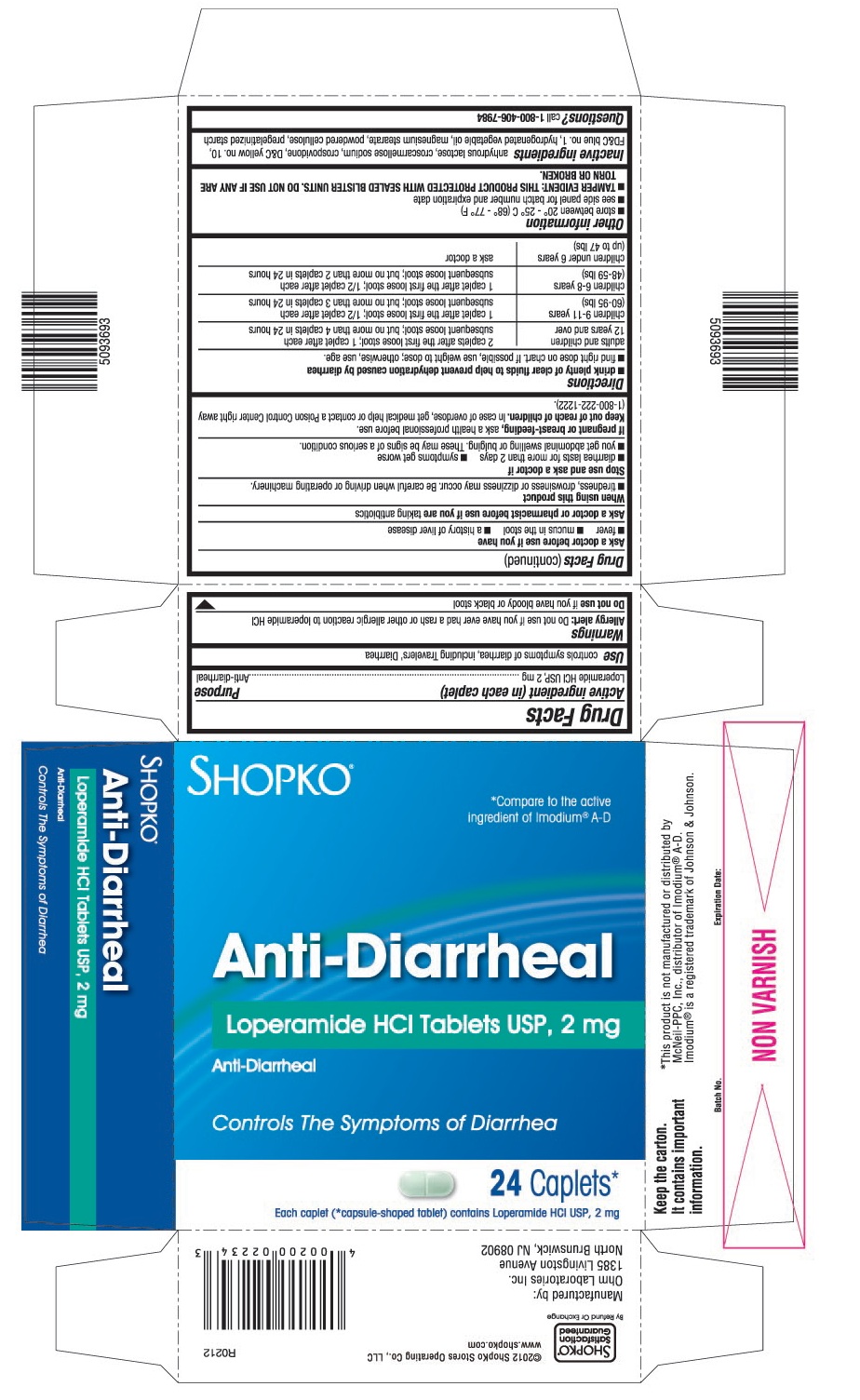 DRUG LABEL: Loperamide Hydrochloride
NDC: 37012-123 | Form: TABLET
Manufacturer: Shopko Stores Operating Co., LLC
Category: otc | Type: HUMAN OTC DRUG LABEL
Date: 20130206

ACTIVE INGREDIENTS: LOPERAMIDE HYDROCHLORIDE 2 mg/1 1
INACTIVE INGREDIENTS: ANHYDROUS LACTOSE; CROSCARMELLOSE SODIUM; CROSPOVIDONE; D&C YELLOW NO. 10; FD&C BLUE NO. 1; TRISTEARIN; MAGNESIUM STEARATE; POWDERED CELLULOSE; STARCH, PREGELATINIZED CORN

Drug Facts

ACTIVE INGREDIENT (IN EACH CAPLET)

Loperamide HCI USP, 2 mg

PURPOSE

Anti-diarrheal

USE

Controls symptoms of diarrhea, including Travelers’ Diarrhea

WARNINGS

Allergy alert: Do not use if you have ever had a rash or other allergic reaction to loperamide HCI

Do not use

If you have bloody or black stool

Ask a doctor before use if you have

- fever
- mucus in the stool
- a history of liver disease

Ask a doctor or pharmacist before use if you are

Taking antibiotics

When using this product

- tiredness, drowsiness or dizziness may occur. Be careful when driving or operating machinery.

Stop use and ask a doctor if

- diarrhea lasts for more than 2 days
- symptoms get worse
- you get abdominal swelling or bulging. These may be signs of a serious condition.

If pregnant or breast-feeding

Ask a health professional before use.

Keep out of reach of children.

In case of overdose, get medical help or contact a Poison Control Center right away (1-800-222-1222).

DIRECTIONS

- drink plenty of clear fluids to help prevent dehydration caused by diarrhea
- find right dose on chart. If possible, use weight to dose; otherwise, use age.
  adults and children 12 years and over | 2 caplets after the first loose stool; 1 caplet after each subsequent loose stool; but no more than 4 caplets in 24 hours
  children 9-11 years (60-95 lbs) | 1 caplet after the first loose stool; ½ caplet after each subsequent loose stool; but no more than 3 caplets in 24 hours
  children 6-8 years (48-59 lbs) | 1 caplet after the first loose stool; ½ caplet after each subsequent loose stool; but no more than 2 caplets in 24 hours
  children under 6 years (up to 47 lbs) | ask a doctor

OTHER INFORMATION

- store between 20° – 25° C (68° – 77° F)
- see side panel for batch number and expiration date
- TAMPER EVIDENT: THIS PRODUCT PROTECTED WITH SEALED BLISTER UNITS. DO NOT USE IF ANY ARE TORN OR BROKEN.

INACTIVE INGREDIENTS

Anhydrous lactose, croscarmellose sodium, crospovidone, D&C yellow no.10, FD&C blue no.1, hydrogenated vegetable oil, magnesium stearate, powdered cellulose, pregelatinized starch

QUESTIONS?

Call 1800-406-7984

PRINCIPAL DISPLAY PANEL

SHOPKO®

* Compare to the active ingredient of Imodium® A-D

Anti-Diarrheal

Loperamide HCl Tablets USP, 2 mg

Anti-Diarrheal

Controls The Symptoms of Diarrhea

24 Caplets*

Each caplet (*capsule-shaped tablet) contains Loperamide HCl USP, 2 mg

Manufactured by: Ohm Laboratories Inc.

5093693/R0212